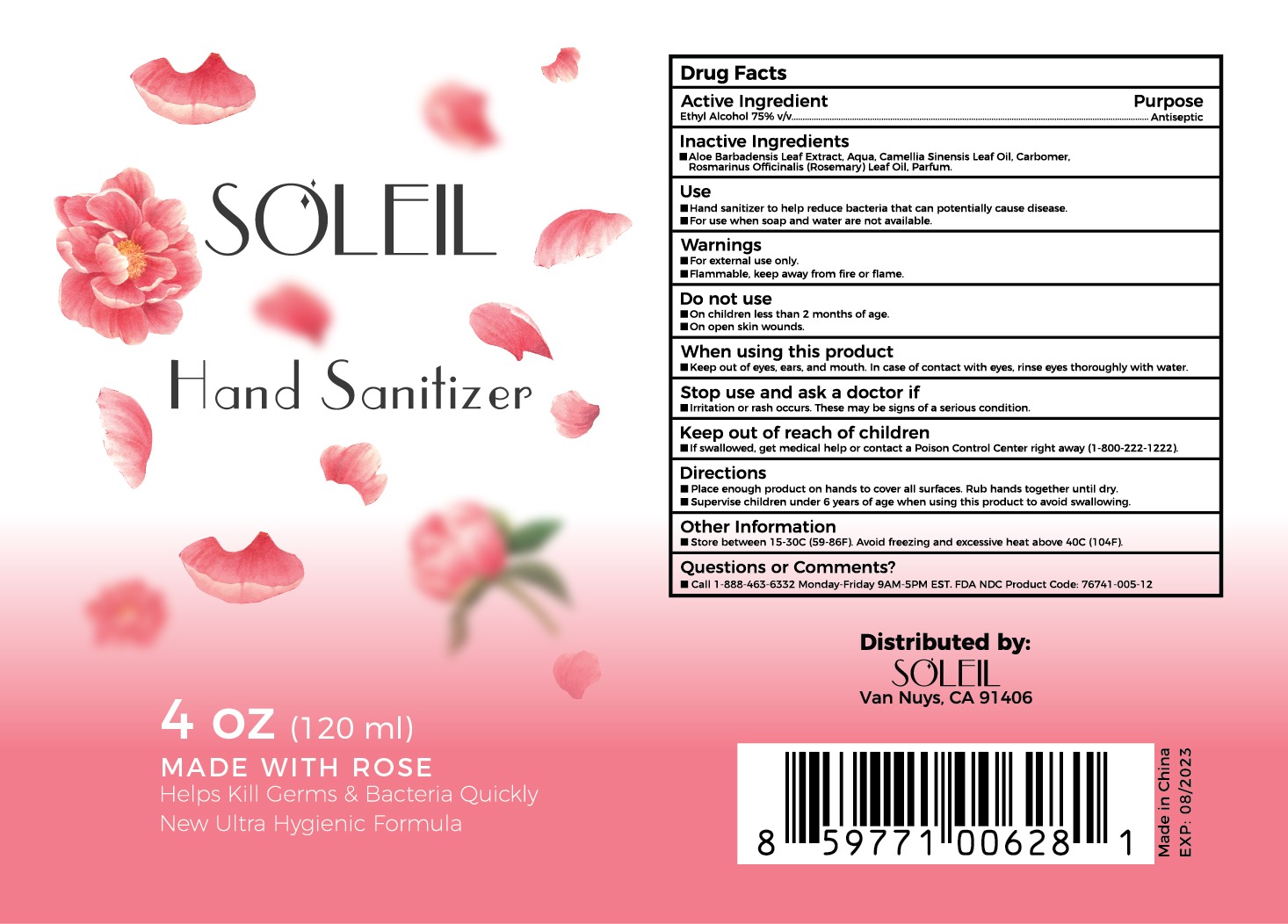 DRUG LABEL: Rose Hand Sanitizer
NDC: 76741-005 | Form: SOLUTION
Manufacturer: Sutra Beauty Inc
Category: otc | Type: HUMAN OTC DRUG LABEL
Date: 20201229

ACTIVE INGREDIENTS: ALCOHOL 75 mL/100 mL
INACTIVE INGREDIENTS: CARBOMER 940; WATER; ROSEMARY OIL; ALOE VERA LEAF; TEA LEAF OIL

Active Ingredient(s)

Ethyl Alcohol 75% v/v.

Purpose

Antiseptic

Inactive ingredients

Aloe Barbadensis Leaf Extract, Aqua, Camellia Sinensis Leaf Oil, Carbomer, Rosmarinus Officinalis (Rosemary) Leaf Oil,
Parfum.

Use

- Hand Sanitizer to help reduce bacteria that can potentially cause disease.
- For use when soap and water are not available.

Warnings

- For external use only.
- Flammable, keep away from fire or flame.

Do not use

- On children less than 2 months of age.
- On open skin wounds.

WHEN USING

Keep out of eyes, ears, and mouth. In case of contact with eyes, rinse eyes thoroughly with water.

STOP USE

Irritation or rash occurs. These may be signs of a serious condition.

KEEP OUT OF REACH OF CHILDREN

- If swallowed, get medical help or contact a Poison Control Center right away (1-800-222-1222).

Directions

- Place enough product on hands to cover all surfaces. Rub hands together until dry.
- Supervise children under 6 years of age when using this product to avoid swallowing.

Other information

- Store between 15-30C (59-86F).
- Avoid freezing and excessive heat above 40C (104F).

Questions or Comments?

- Call 1-888-463-6332 Monday-Friday 9AM-5PM EST. FDA NDC Product Code: 76741-005-12

Package Label - Principal Display Panel

120 ml NDC: 76741-005-12